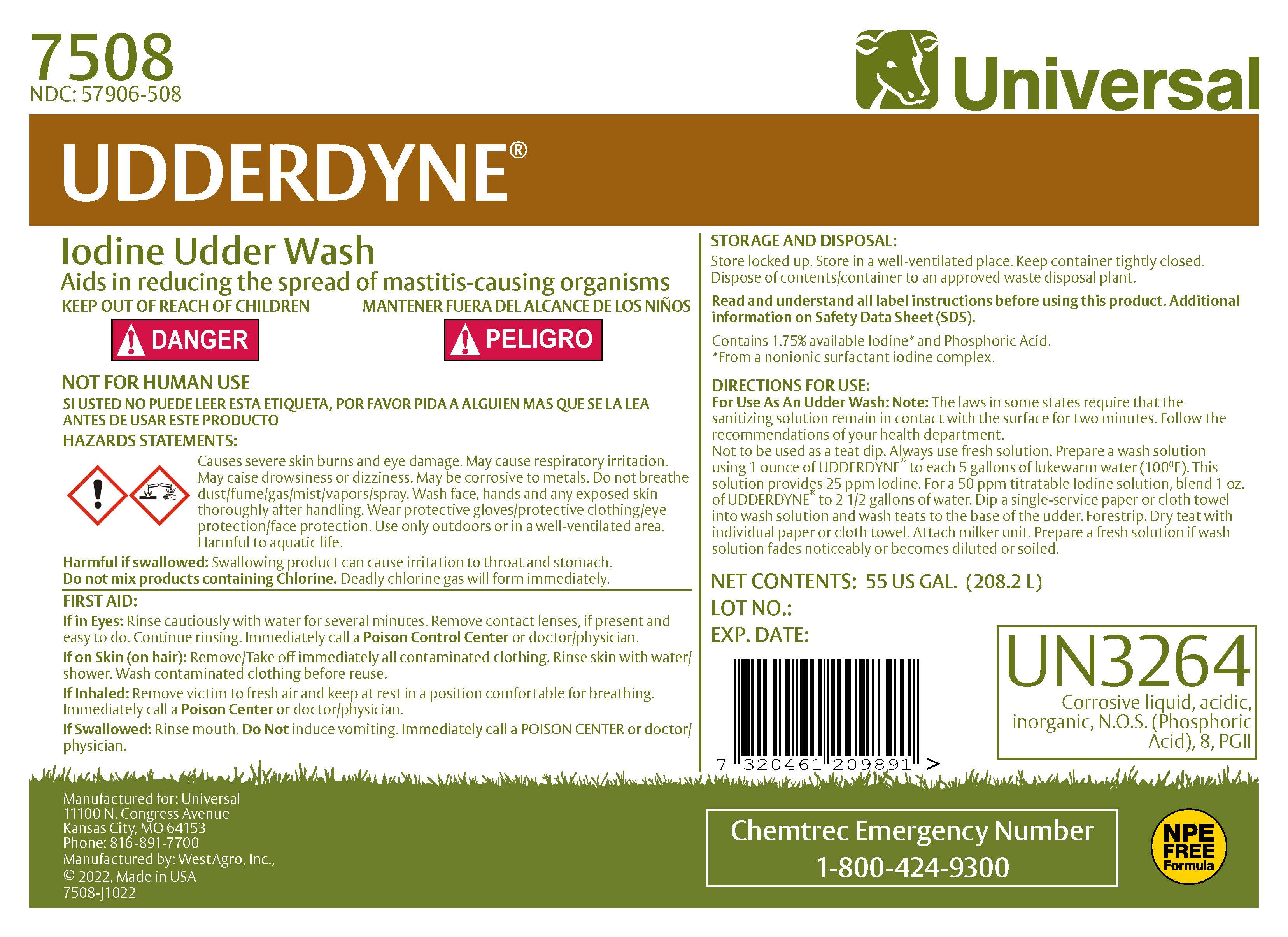 DRUG LABEL: UdderDyne
NDC: 57906-508 | Form: SOLUTION
Manufacturer: Universal
Category: animal | Type: OTC ANIMAL DRUG LABEL
Date: 20240920

ACTIVE INGREDIENTS: IODINE 18.3 g/1 L

UDDERDYNE

7508

NDC: 57906-508

ACTIVE INGREDIENT

Iodine Udder Wash

Contains 1.75% available Iodine* and Phosphoric Acid
*From a nonionic surfactant iodine complex.

INDICATIONS AND USAGE

Aids in reducing the spread of mastitis-causing organisms

DIRECTIONS FOR USE:
FOR USE AS AN UDDER WASH:
NOTE: The laws in some states require that the sanitizing solution remain in contact with the surface for two minutes. Follow the recommendations of your health department.

Not to be used as a teat dip. Always use fresh solution. Prepare a wash solution using 1 ounce of UDDERDYNE® to each 5 gallons of lukewarm water (100° F). This solution provides 25 ppm Iodine. For a 50 ppm titratable Iodine solution, blend 1 oz. of UDDERDYNE® to 2 1/2 gallons of water. Dip a single service paper or cloth towel into wash solution and wash teats to the base of the udder. Forestrip. Dry teat with individual paper or cloth towel. Attach milker unit. Prepare a fresh solution if wash solution fades noticeably or becomes diluted or soiled.

STORAGE AND DISPOSAL:
Store locked up. Store in a well-ventilated place. Keep container tightly closed. Dispose of contents/container to an approved waste disposal plant.

KEEP OUT OF REACH OF CHILDREN

!DANGER

NOT FOR HUMAN USE

HAZARDSSTATEMENTS:
Causes severe skin burns and eye damage. May cause respiratory irritation. May cause drowsiness or dizziness. May be corrosive to metals. Do not breathe dust/fume/gas/mist/vapor/spray. Wash face, hands and any exposed skin thoroughly after handling. Wear protective gloves/protective clothing/eye protection/face protection. Use only outdoors or in a well-ventilated area. Harmful to aquatic life.
Harmful if swallowed. Swallowing product can cause irritation to throat and stomach.
Do not mix products containing Chlorine. Deadly Chlorine gas will form immediately.

FIRST AID:
If in Eyes: Rinse cautiosly with water for several minutes. Remove contact lenses, if present, and easy to do. Continue rinsing. Immediately call Poison Control Center or doctor/physician.

If on Skin (on hair): Remove/Take off immediately all contaminated clothing. Rinse skin with water/shower. Wash contaminated clothing before reuse.

If Inhaled: Remove victim to fresh air and keep at rest in a position comfortable for breathing. Immediately call a Poison Center or doctor/physician.

If Swallowed: Rinse mouth. Do Not induce vomiting. Immediately call a POISON CENTER or doctor/physician.

UN3264

Corrosive liquid, acidic, inorganic, N.O.S. (Phosphoric Acid), 8,PGll

Read and understand all label instructions before using this product. Additional information on Safety Data Sheet (SDS).

Chemtrec Emergency Number

1-800-424-9300

PACKAGE LABEL

Add image transcription here...